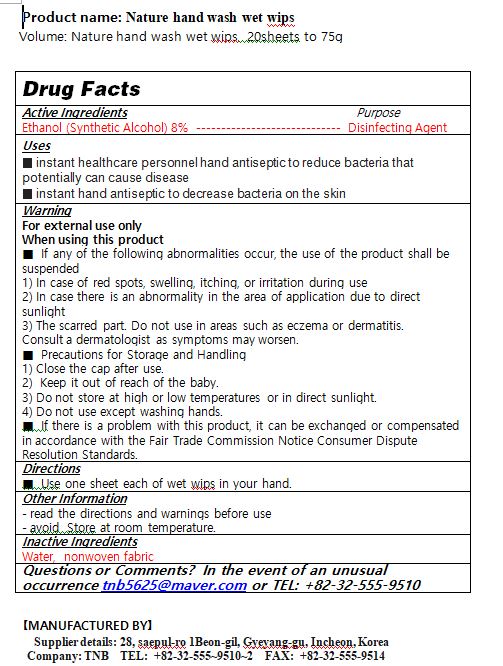 DRUG LABEL: Nature hand wash wet wipes
NDC: 80081-0001 | Form: LIQUID
Manufacturer: TNB Networks Co., Ltd.
Category: otc | Type: HUMAN OTC DRUG LABEL
Date: 20200824

ACTIVE INGREDIENTS: ALCOHOL 8 g/100 g
INACTIVE INGREDIENTS: GLYCERIN; BUTYLENE GLYCOL; DIPROPYLENE GLYCOL

ACTIVE INGREDIENT

alcohol

INACTIVE INGREDIENT

Dihydrogen Oxid
Alcohol
Glycerin
Dipropyene Glycol
Sodium Hyaluronate
Butylene Glycol
Centella asiatica Extract
Camellia sinensis Leaf Extract
Aloe barbadensis Leaf Extract
Portulaca Oleracea Exract
Peppermint
Disodium EDTA
Chlorphenesin
Phenoxyethanol

PURPOSE

■ instant healthcare personnel hand antiseptic to reduce bacteria that potentially can cause disease

■ instant hand antiseptic to decrease bacteria on the skin

keep out of reach of the children

INDICATIONS AND USAGE

■ Use one sheet each of wet wips in your hand.

WARNINGS

For external use only

When using this product

■ If any of the following abnormalities occur, the use of the product shall be suspended

1) In case of red spots, swelling, itching, or irritation during use

2) In case there is an abnormality in the area of application due to direct sunlight

3) The scarred part. Do not use in areas such as eczema or dermatitis.

Consult a dermatologist as symptoms may worsen.

■ Precautions for Storage and Handling

1) Close the cap after use.

2) Keep it out of reach of the baby.

3) Do not store at high or low temperatures or in direct sunlight.

4) Do not use except washing hands.

■ If there is a problem with this product, it can be exchanged or compensated in accordance with the Fair Trade Commission Notice Consumer Dispute Resolution Standards.

DOSAGE AND ADMINISTRATION

for external use only